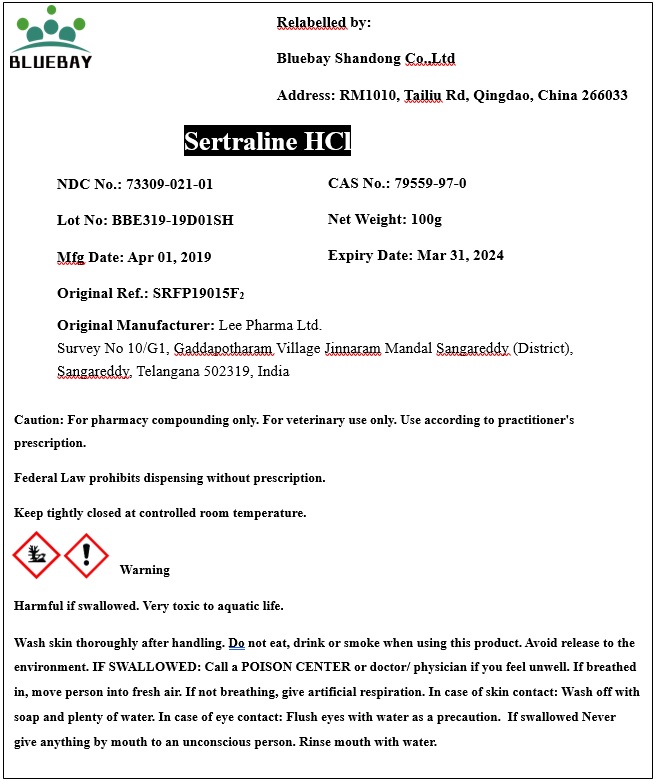 DRUG LABEL: Sertraline HCl
NDC: 73309-021 | Form: POWDER
Manufacturer: BLUEBAY SHANDONG CO.,LTD
Category: other | Type: BULK INGREDIENT
Date: 20190822

ACTIVE INGREDIENTS: SERTRALINE HYDROCHLORIDE 1 g/1 g

Sertraline HCl